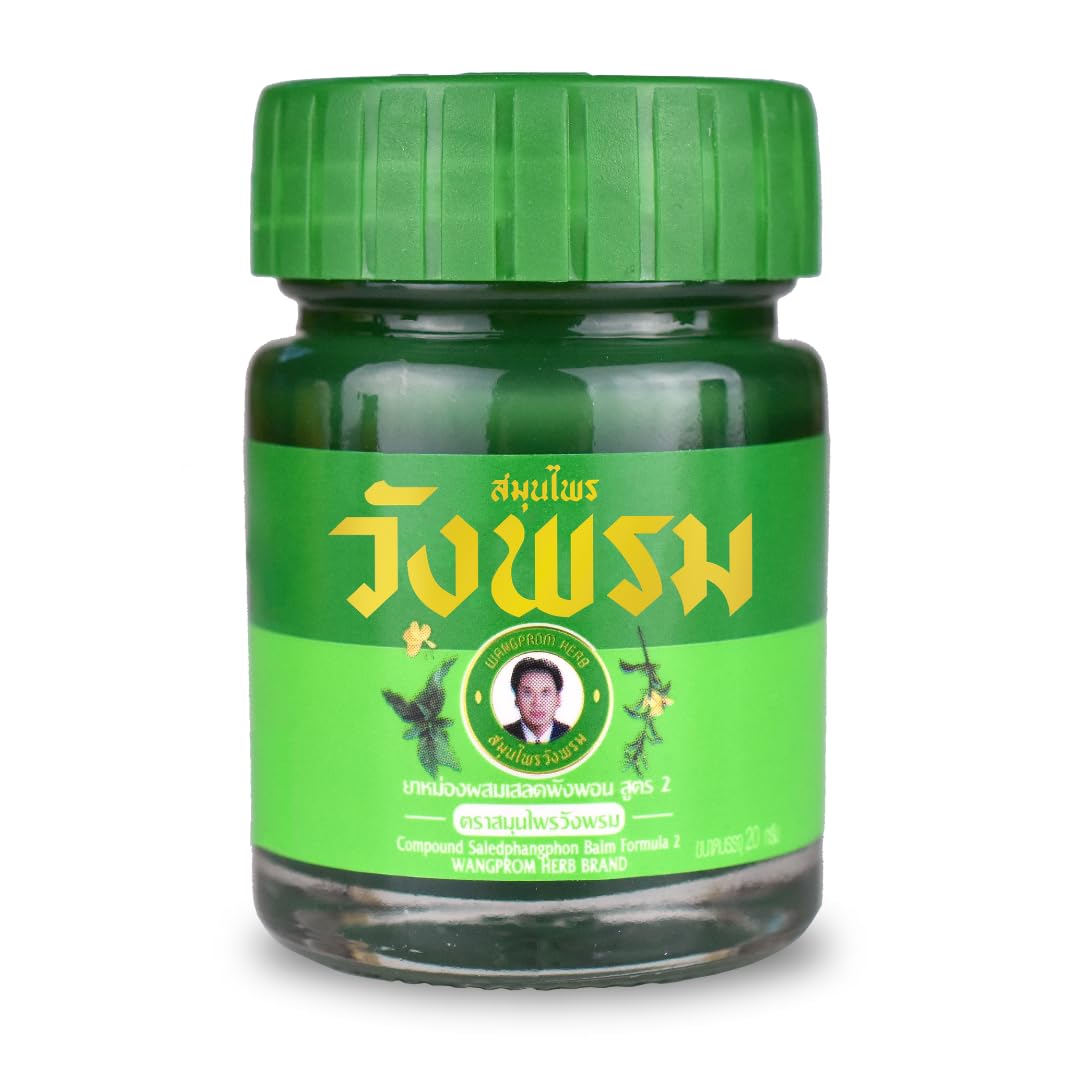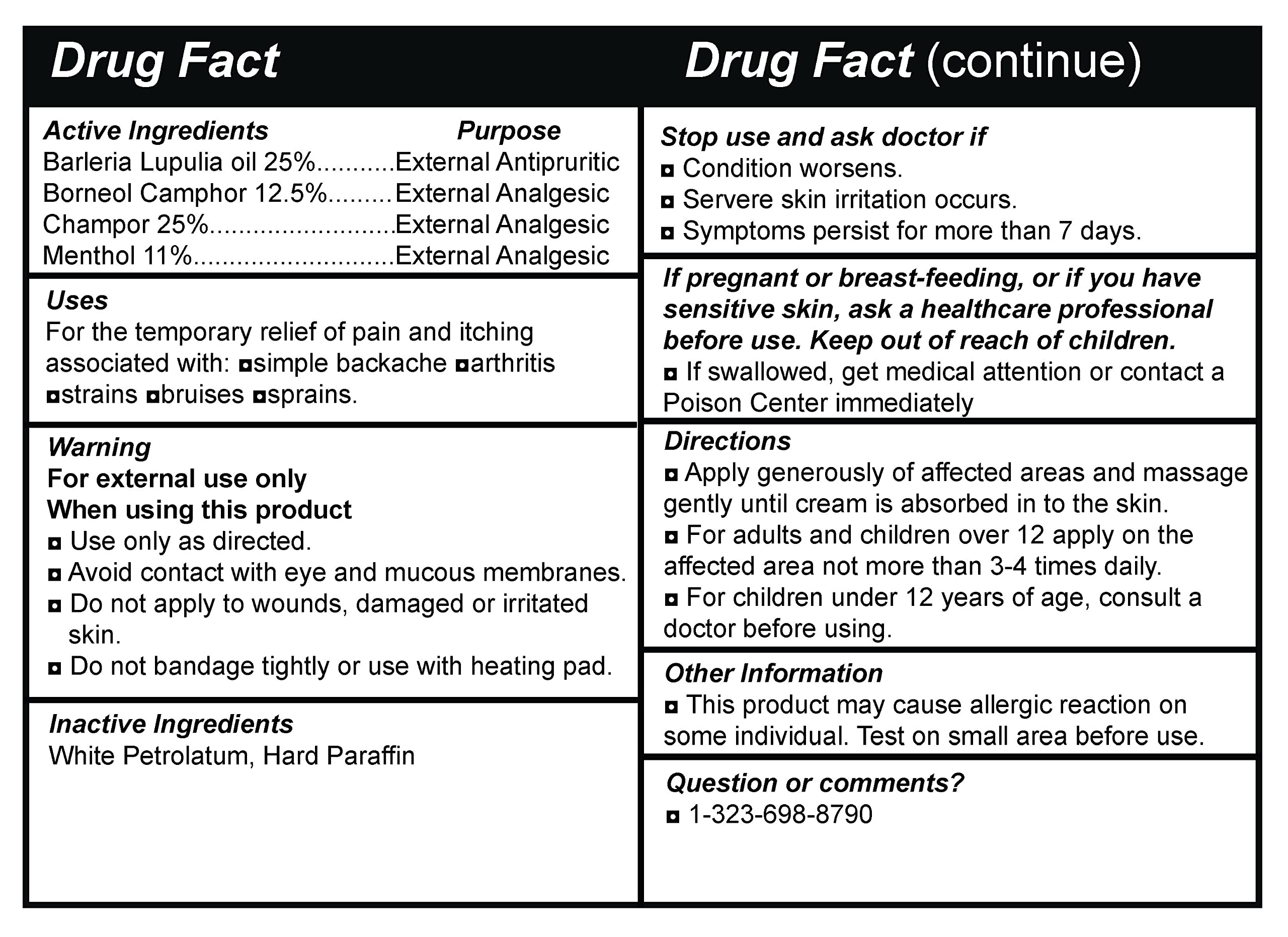 DRUG LABEL: Wang Prom Green Balm by Wang Prom
NDC: 84212-444 | Form: PATCH
Manufacturer: AMBIENCE FAMILY INC
Category: otc | Type: HUMAN OTC DRUG LABEL
Date: 20260202

ACTIVE INGREDIENTS: MENTHOL 5.5 g/100 g; BORNEOL 6.25 g/100 g; CINNAMOMUM CAMPHORA LEAF 12.5 g/100 g; BARLERIA LUPULINA WHOLE 12.5 g/100 g
INACTIVE INGREDIENTS: PARAFFIN; WHITE PETROLATUM

DOSAGE AND ADMINISTRATION

Uses For the temporary relief of pain and itching associated with: asimple backache aarthritis nstrains abruises nsprains.

WARNINGS

Warning For external use only When using this product a Use only as directed. a Avoid contact with eye and mucous membranes. a Do not apply to wounds, damaged or irritated skin. a Do not bandage tightly or use with heating pad.

Inactive Ingredients White Petrolatum, Hard Paraffin

INDICATIONS AND USAGE

Uses For the temporary relief of pain and itching associated with: asimple backache aarthritis nstrains abruises nsprains.

Directions a Apply generously of affected areas and massage gently until cream is absorbed in to the skin. a For adults and children over 12 apply on the affected area not more than 3-4 times daily. a For children under 12 years of age, consult a doctor before using.

Other Information a This product may cause allergic reaction on some individual. Test on small area before use.

Keep out of reach of children. a If swallowed, get medical attention or contact a Poison Center immediately

PURPOSE

Uses For the temporary relief of pain and itching associated with: asimple backache aarthritis nstrains abruises nsprains.

ACTIVE INGREDIENT

Active Ingredients Purpose Barleria Lupulia oil 25% External Antipruritic Borneo! Camphor 12.5% External Analgesic Champor 25% External Analgesic Menthol 11% External Analgesic

PACKAGE LABEL

Drug Fact Drug Fact (continue)
Active Ingredients Purpose Barleria Lupulia oil 25% External Antipruritic Borneo! Camphor 12.5% External Analgesic Champor 25% External Analgesic Menthol 11% External Analgesic
Uses For the temporary relief of pain and itching associated with: asimple backache aarthritis nstrains abruises nsprains.
Warning For external use only When using this product a Use only as directed. a Avoid contact with eye and mucous membranes. a Do not apply to wounds, damaged or irritated skin. a Do not bandage tightly or use with heating pad.
Inactive Ingredients White Petrolatum, Hard Paraffin
Stop use and ask doctor if a Condition worsens. Servere skin irritation occurs. a Symptoms persist for more than 7 days.
If pregnant or breast-feeding, or if you have sensitive skin, ask a healthcare professional before use. Keep out of reach of children. a If swallowed, get medical attention or contact a Poison Center immediately
Directions a Apply generously of affected areas and massage gently until cream is absorbed in to the skin. a For adults and children over 12 apply on the affected area not more than 3-4 times daily. a For children under 12 years of age, consult a doctor before using.
Other Information a This product may cause allergic reaction on some individual. Test on small area before use.
Question or comments? a 1-323-698-8790